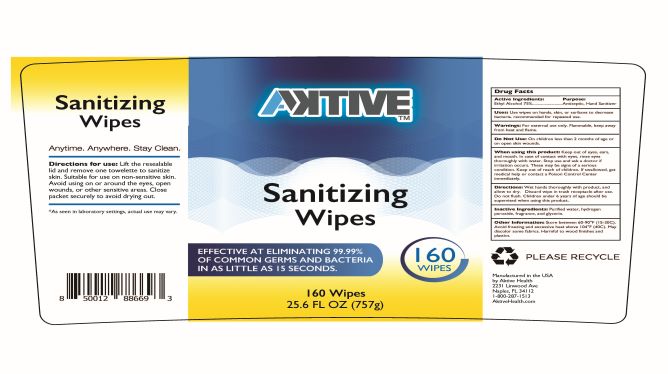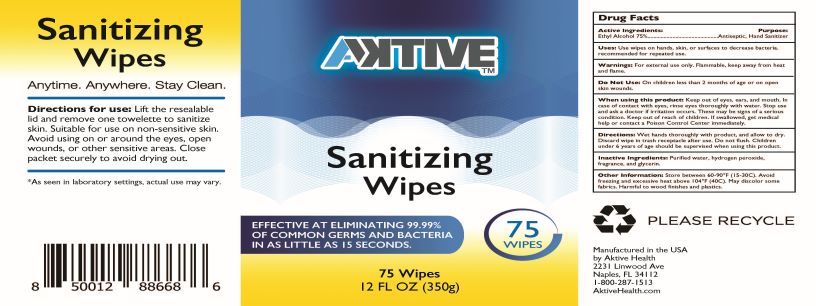 DRUG LABEL: Aktive Sanitizing Wipes
NDC: 81156-001 | Form: CLOTH
Manufacturer: Hall Global LLC
Category: otc | Type: HUMAN OTC DRUG LABEL
Date: 20201123

ACTIVE INGREDIENTS: ALCOHOL 75 mL/100 mL
INACTIVE INGREDIENTS: FRAGRANCE LEMON ORC2001060 1 mL/100 mL; GLYCERIN 1.45 mL/100 mL; HYDROGEN PEROXIDE 0.125 mL/100 mL; WATER

Wipe

This is a hand sanitizer manufactured according to the Temporary Policy for Preparation of Certain Alcohol-Based Hand Sanitizer Products During the Public Health Emergency (CoViD-19); Guidance for Industry.

The hand sanitizer is manufactured using only the following United States Pharmacopoeia (USP) grade ingredients in the preparation of the product (percentage in final product formulation) consistent with World Health Organization (WHO) recommendations:

1. Ethyl Alcohol (75%, v/v) in an aqueous solution denatured according to Alcohol and Tobacco Tax and Trade Bureau regulations in 27 CFR part 20.
2. Glycerin (1.45% v/v).
3. Hydrogen peroxide (0.125% v/v).
4. Sterile distilled water or boiled cold water\
5. Fragrance

The firm does not add other active or inactive ingredients. Different or additional ingredients may impact the quality and potency of the product.

Active Ingredient(s)

Ethyl Alcohol 75% v/v. Purpose: Antiseptic

Purpose

Antiseptic, Hand Sanitizer

Use

Use wipes on hands, skin, or surfaces to decrease bacteria, recomended for repeated use.

Warnings

For external use only. Flammable. Keep away from heat or flame

Do not use

- in children less than 2 months of age
- on open skin wounds

WHEN USING

Keep out of eyes, ears, and mouth. In case of contact with eyes, rinse eyes thoroughly with water.

Stop use and ask a doctor if irritation or rash occurs. These may be signs of a serious condition.
Keep out of reach of children. If swallowed, get medical help or contact a Poison Control Center immediately

Stop use and ask a doctor if irritation or rash occurs. These may be signs of a serious condition.

Keep out of reach of children. If swallowed, get medical help or contact a Poison Control Center right away.

Directions

Wet hands thoroughtly with product, and allow to dry. Discard wipe in trash receptacle after use. Do not flush. Children under 6 years of age should be supervised when using this product.

Other information

- Store between 60-90 F (15-30C)
- Avoid freezing and excessive heat above 104 F(40C). May discolor some fabrics. Harmful to wood finishes and plastics.

Inactive ingredients

glycerin, hydrogen peroxide, purified water, fragrance